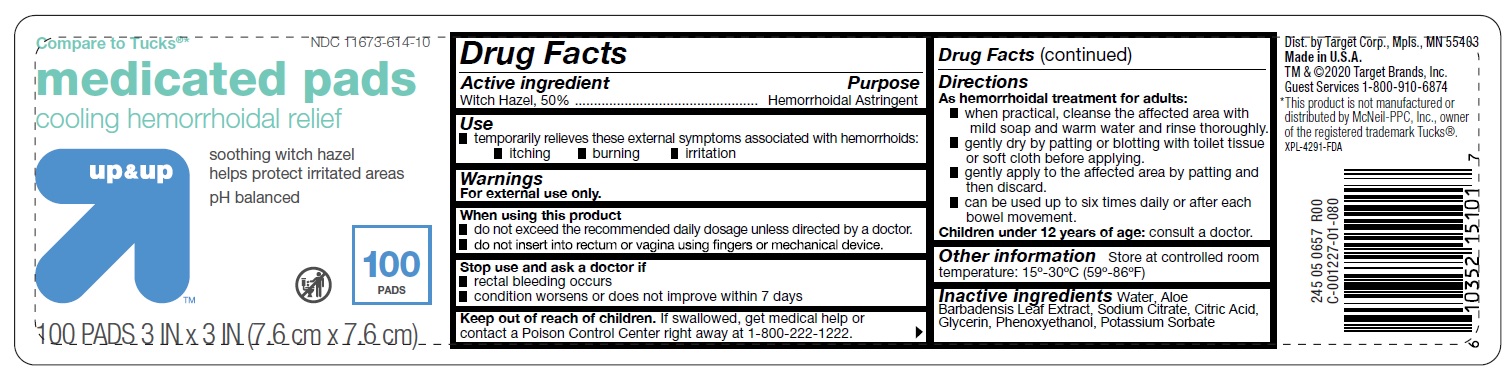 DRUG LABEL: medicated pads
NDC: 11673-614 | Form: PATCH
Manufacturer: TARGET CORPORATION
Category: otc | Type: HUMAN OTC DRUG LABEL
Date: 20251014

ACTIVE INGREDIENTS: WITCH HAZEL 50 mg/100 mg
INACTIVE INGREDIENTS: WATER; ALOE VERA LEAF; SODIUM CITRATE; CITRIC ACID MONOHYDRATE; GLYCERIN; PHENOXYETHANOL; POTASSIUM SORBATE

Drug Facts

Active Ingredient

Witch Hazel 50%

Purpose

Hemorrhoidal Astringent

Uses

Temporarily relieves these external symptoms associated with hemorrhoids:

- itching
- burning
- irritation

Warnings

For external use only.

When using this product

- do not exceed the recommended daily dosage unless directed by a doctor.
- do not insert into rectum or vagina using fingers or mechanical device.

Stop use and ask a doctor if

- rectal bleeding occurs
- condition worsens or does not improve within 7 days.

Keep out of reach of children.

If swallowed, get medical help or contact a Poison Control Center right away at 1-800-222-1222.

Directions

As hemorrhoidal treatment for adults:

- when practical, cleanse the affected area with mild soap and warm water and rinse thoroughly.
- gently dry by patting or blotting with toilet tissue or soft cloth before applying.
- gently apply to the affected area by patting and then discard.
- can be used up to six times daily or after each bowel movement.

Children under 12 years of age

- consult a doctor.

Other Information

Store at controlled room temperature: 15º-30ºC (59º-86ºF)

Inactive Ingredients

Water, Aloe Barbadensis Leaf Extract, Sodium Citrate, Citric Acid, Glycerin, Phenoxyethanol, Potassium Sorbate

Principal Display Panel

NDC 11673-614-10

Compare to Tucks®*

medicated pads

cooling hemmorhoidal relief

soothing witch hazel helps protect irritated areas

pH balanced

100 PADS

3 IN X 3 IN (7.6 cm X 7.6 cm)